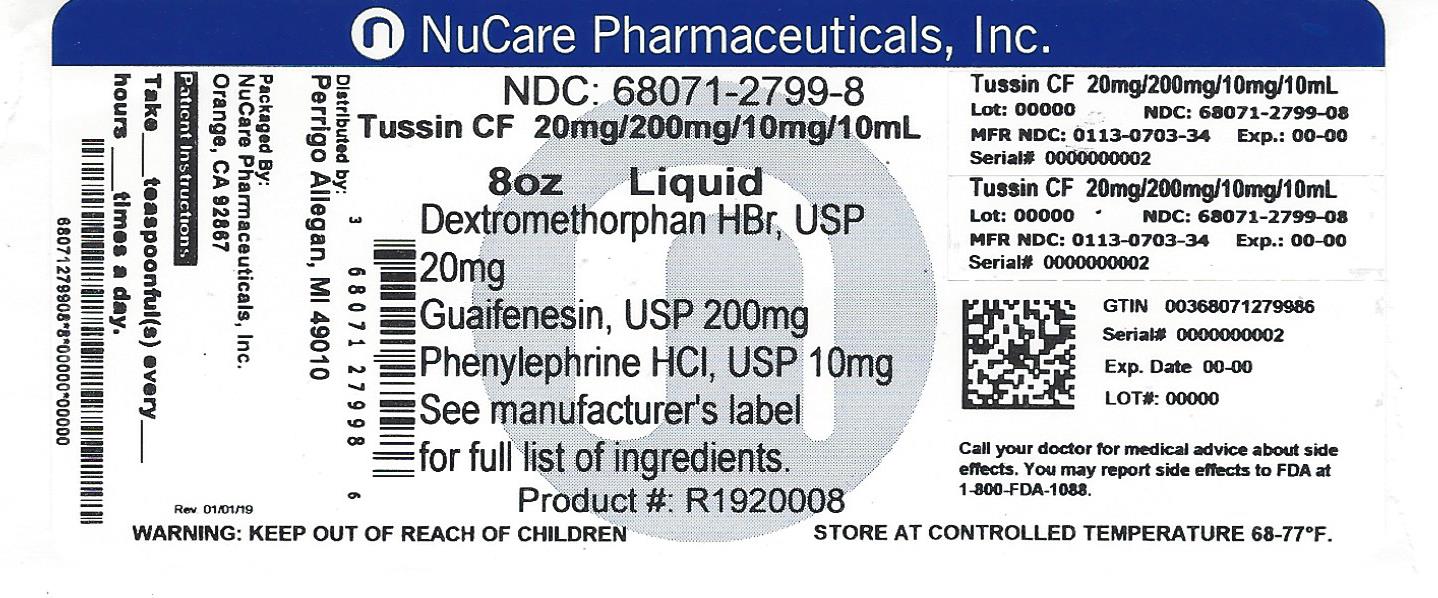 DRUG LABEL: Tussin CF
NDC: 68071-2799 | Form: SOLUTION
Manufacturer: NuCare Pharmaceuticals,Inc.
Category: otc | Type: HUMAN OTC DRUG LABEL
Date: 20220719

ACTIVE INGREDIENTS: DEXTROMETHORPHAN HYDROBROMIDE 20 mg/10 mL; GUAIFENESIN 200 mg/10 mL; PHENYLEPHRINE HYDROCHLORIDE 10 mg/10 mL
INACTIVE INGREDIENTS: ANHYDROUS CITRIC ACID; EDETATE DISODIUM; FD&C RED NO. 40; GLYCERIN; PROPYLENE GLYCOL; WATER; SODIUM BENZOATE; SODIUM CITRATE, UNSPECIFIED FORM; SORBITOL; SUCRALOSE

Perrigo Tussin CF Drug Facts

Active ingredients (in each 10 mL)

Dextromethorphan HBr, USP 20 mg

Guaifenesin, USP 200 mg

Phenylephrine HCl, USP 10 mg

Purposes

Cough suppressant

Expectorant

Nasal decongestant

Uses

- helps loosen phlegm (mucus) and thin bronchial secretions to drain bronchial tubes
- temporarily relieves these symptoms occurring with a cold:
- nasal congestion
- cough due to minor throat and bronchial irritation

Warnings

Do not use

- if you are now taking a prescription monoamine oxidase inhibitor (MAOI) (certain drugs for depression, psychiatric, or emotional conditions, or Parkinson's disease), or for 2 weeks after stopping the MAOI drug. If you do not know if your prescription drug contains an MAOI, ask a doctor or pharmacist before taking this product.

Ask a doctor before use if you have

- heart disease
- high blood pressure
- thyroid disease
- diabetes
- trouble urinating due to an enlarged prostate gland
- cough that occurs with too much phlegm (mucus)
- cough that lasts or is chronic such as occurs with smoking, asthma, chronic bronchitis or emphysema

When using this product

do not use more than directed

Stop use and ask a doctor if

- you get nervous, dizzy, or sleepless
- symptoms do not get better within 7 days or are accompanied by fever
- cough lasts more than 7 days, comes back, or is accompanied by fever, rash, or persistent headache. A persistent cough may be a sign of a serious condition.

If pregnant or breast-feeding,

ask a health professional before use.

Keep out of reach of children.

In case of overdose, get medical help or contact a Poison Control Center right away (1-800-222-1222).

Directions

- do not take more than 6 doses in any 24-hour period
- measure only with dosing cup provided
- keep dosing cup with product
- mL = milliliter
- this adult product is not intended for use in children under 12 years of age

age | dose
adults and children 12 years and over | 10 mL every 4 hours
children under 12 years | do not use

Other information

- each 10 mL contains: sodium 5 mg
- store at 20-25ºC (68-77ºF).
- Do not refrigerate.

Inactive ingredients

anhydrous citric acid, edetate disodium, FD&C red no. 40, flavor, glycerin, propylene glycol, purified water, sodium benzoate, sodium citrate, sorbitol solution, sucralose

Questions or comments?

1-800-719-9260